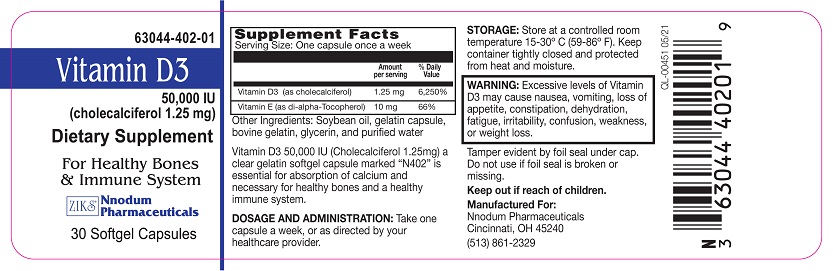 DRUG LABEL: VITAMIN D3 1.25 MG 50000 IU
NDC: 63044-402 | Form: CAPSULE, GELATIN COATED
Manufacturer: Nnodum Pharmaceuticals
Category: other | Type: DIETARY SUPPLEMENT
Date: 20210527

ACTIVE INGREDIENTS: CHOLECALCIFEROL 1.25 mg/1 1; .ALPHA.-TOCOPHEROL, D- 10 mg/1 1
INACTIVE INGREDIENTS: SOYBEAN OIL; GLYCERIN; GELATIN TYPE B BOVINE (230 BLOOM); WATER

VITAMIN D3 1.25MG (50,000IU) Dietary Supplement

Statement of Identity

VITAMIN D3 1.25MG (50,000IU) Softgel Capsule

CHOLECALCIFEROL, USP (50,000IU)
Vitamin E- D-alpha Tocopherol 10mg (1000IU)

Warnings

WARNINGS: Vitamin D3 is a high Potency dietary supplement. Do not exceed recommended dosage. Not recommended for children, pregnant or lactating women, or individuals with liver disease, and those taking thiazide diuretics may be at greater risk of toxicity.

Dosage & Administration

DIRECTIONS: Take 0ne (1) capsule each week, or as directed by your physician.

Take with food. Store in cool dry place. Protect from light.

Precautions/Warning

These statements have not been evaluated by the Food and Drug Administration.

This product is not intended to diagnose, treat, cure or prevent any disease.

Storage

Store in cool dry place. Protect from light.

Health Claims

DIETARY SUPPLEMENT

Vitamin D3 50,000 IU is essential for absorption of calcium and necessary for healthy bones and a healthy immune system.

Vitamin D3 Product Label

NDC 63044-402-01
VITAMIN D3 1.25MG (50,000IU) Softgel Capsule
CHOLECALCIFEROL, USP (50,000IU)
Vitamin E- D-alpha Tocopherol 10mg (1000IU)

DIETARY SUPPLEMENT

Vitamin D3 50,000 IU is essential for absorption of calcium and necessary for healthy bones and a healthy immune system.

WARNINGS: Vitamin D3 is a high Potency dietary supplement. Do not exceed recommended dosage. Not recommended for children, pregnant or lactating women, or individuals with liver disease, and those taking thiazide diuretics may be at greater risk of toxicity.

DESCRIPTION
Vitamin D3 (Cholecalciferol) is a clear gelatin softgel capsule marked “N402”. Vitamin D3 is a fat-soluble high potency vitamin that helps your body absorb calcium and phosphorus. Cholecalciferol is a softgel capsule, colorless crystal, insoluble in water, soluble in organic solvents, and slightly soluble in vegetable oils. It is affected by air and by light. One Unit of vitamin D3 is equivalent to one International Unit (IU). Each softgel capsule, for oral administration, contains Cholecalciferol, 1.25 mg (equivalent to 50,000 USP units of Vitamin D).

Other Ingredients: Soybean oil, Glycerin, Bovine Gelatin and Purified water.

DIRECTIONS: Take 0ne (1) capsule each week, or as directed by your physician. Take with food.

Store in cool dry place. Protect from light.

INDICATIONS AND USAGE
Cholecalciferol Softgel capsule is essential for absorption of calcium and necessary for healthy and strong bones. .

CONTRAINDICATIONS
Cholecalciferol softgel capsules are contraindicated in patients with hypercalcemia, malabsorption syndrome, abnormal sensitivity to the toxic effects of vitamin D, and hypervitaminosis D.
Keep out of the reach of children.

DIRECTIONS: Take 0ne (1) capsule each week, or as directed by your physician. Take with food. Store in cool dry place. Protect from light.

Supplement Facts *
Serving Size: One Softgel Capsule
Each softgel capsule Contains: Vitamin D31.25mg (Cholecalciferol) 50,000 IU and Vitamin E- D-alpha Tocopherol 10mg (1000IU)

HOW SUPPLIED
Bottle of 30 softgel capsule (NDC 63044-402-01).

Store at 20°– 25°C (68°–77°F) [See USP Controlled Room Temperature].
Protect from light and moisture.
Dispense in a tight, light-resistant container as defined in the USP.

These statements have not been evaluated by the Food and Drug Administration. This product is not intended to diagnose, treat, cure or prevent any disease.

Manufactured For:
Nnodum Pharmaceuticals Corp.
Cincinnati, Ohio 45240
United States of America
www.nnodumpharma.com

res